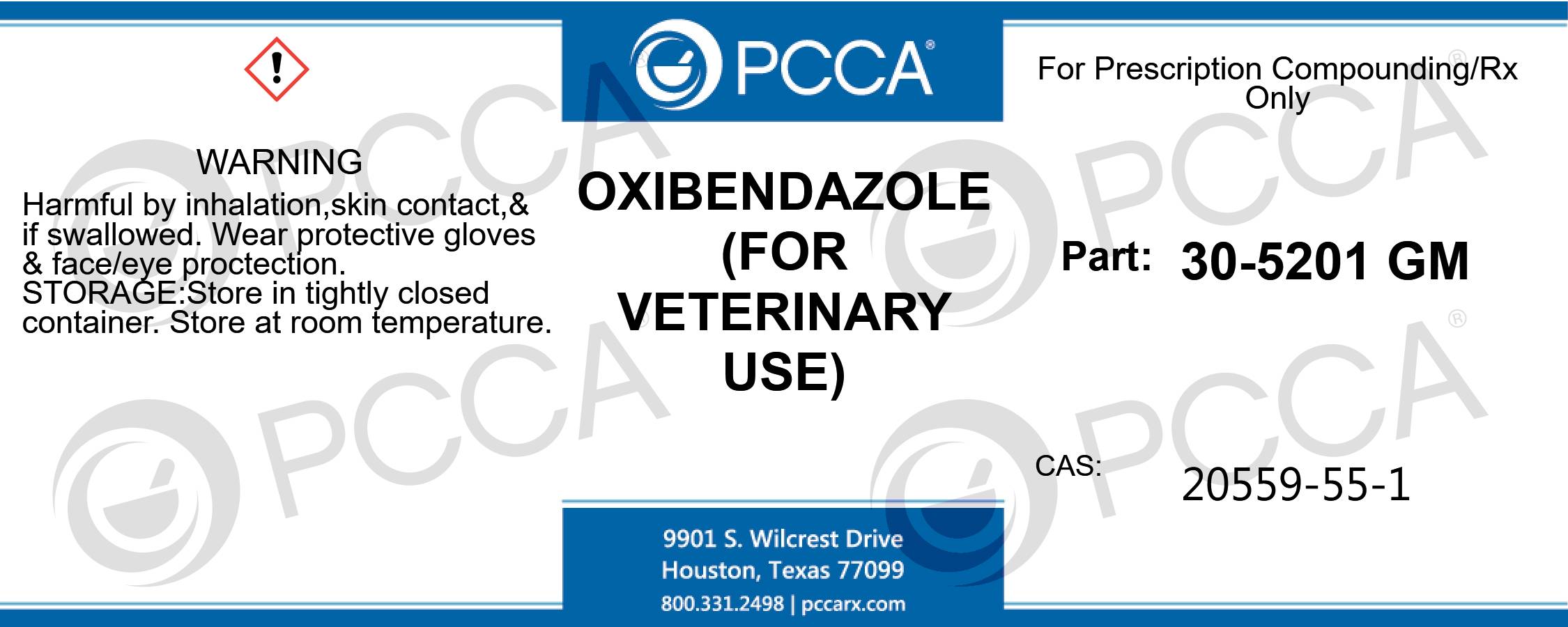 DRUG LABEL: OXIBENDAZOLE
NDC: 51927-5201 | Form: POWDER
Manufacturer: Professional Compounding Centers of America
Category: other | Type: BULK INGREDIENT - ANIMAL DRUG
Date: 20230112

ACTIVE INGREDIENTS: OXIBENDAZOLE 1 kg/1 kg

30-5201 Oxibendazole

OXIBENDAZOLE (FOR VETERINARY USE ONLY) FOR PRESCRIPTION COMPOUNDING/RX ONLY PART: 30-5021 CAS: 20559-55-1 WARNING: HARMFUL BY INHALATION, SKIN CONTACT & IF SWALLOWED. WEAR PROTECTIVE GLOVES & FACE/EYE PROTECTION. Storage: STORE IN TIGHTLY CLOSED CONTAINER. STORE AT ROOM TEMPERATURE.

OXIBENDAZOLE (FOR VETERINARY USE ONLY)
FOR PRESCRIPTION COMPOUNDING/RX ONLY
PART: 30-5021
CAS: 20559-55-1
WARNING:
HARMFUL BY INHALATION, SKIN CONTACT & IF SWALLOWED. WEAR PROTECTIVE GLOVES & FACE/EYE PROTECTION.
Storage: STORE IN TIGHTLY CLOSED CONTAINER. STORE AT ROOM TEMPERATURE.